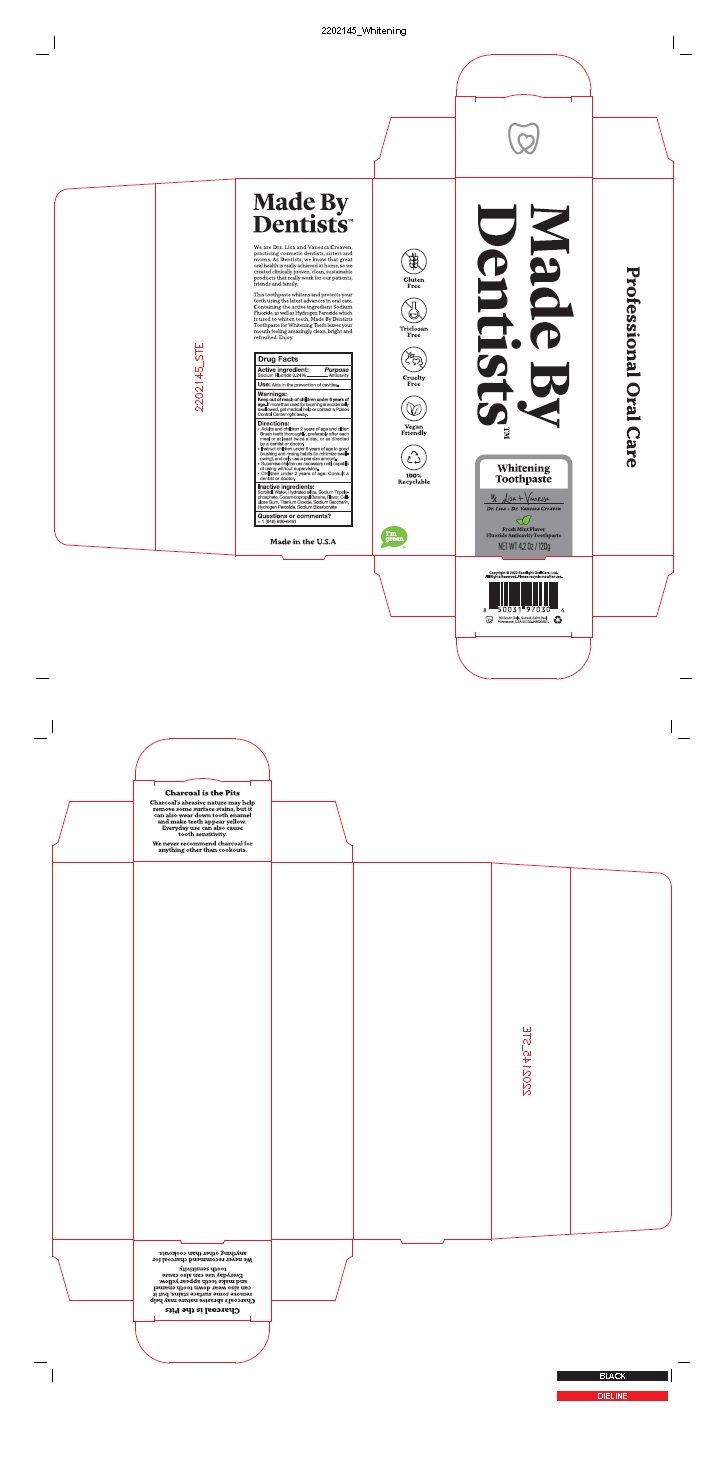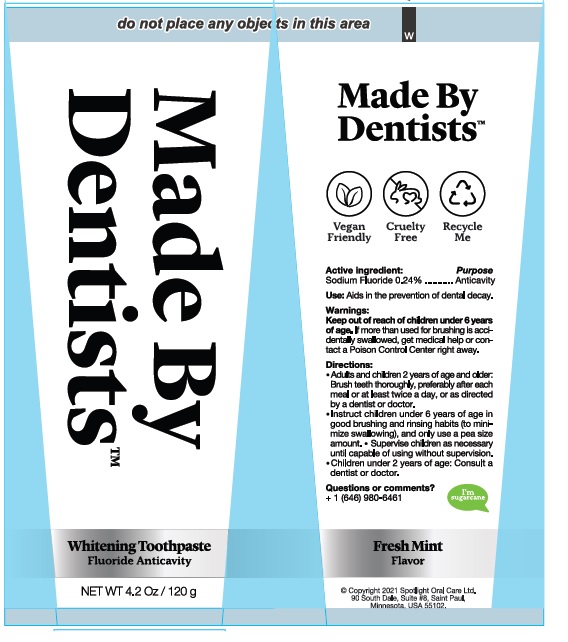 DRUG LABEL: Made By Dentists Whitening
NDC: 75065-015 | Form: PASTE
Manufacturer: Oral Spotlight Care Inc
Category: otc | Type: HUMAN OTC DRUG LABEL
Date: 20220722

ACTIVE INGREDIENTS: SODIUM FLUORIDE 0.24 g/100 g
INACTIVE INGREDIENTS: SORBITOL; WATER; HYDRATED SILICA; SODIUM TRIPOLYPHOSPHATE; COCAMIDOPROPYL BETAINE; CARBOXYMETHYLCELLULOSE SODIUM, UNSPECIFIED; TITANIUM DIOXIDE; SACCHARIN SODIUM; HYDROGEN PEROXIDE; SODIUM BICARBONATE

Made By Dentists™ Whitening Toothpaste

Drug Facts

Active ingredient: Sodium Fluoride 0.24%

Purpose: Anticavity

INDICATIONS AND USAGE

Use: Aids in the prevention of cavities.

Warnings:

Keep out of reach of children under 6 years of age. If
more than used for brushing is accidentally swallowed, get
medical help or contact a Poison Control Center right away.

Directions
• Adults and children 2 years of age and older:
Brush teeth thoroughly, preferably after each
meal or at least twice a day, or as directed
by a dentist or doctor.
• Instruct children under 6 years of age in good
brushing and rinsing habits (to minimize swall-
owing), and only use a pea size amount.
• Supervise children as necessary until capable
of using without supervision.
• Children under 2 years of age: Consult a
dentist or doctor.

Inactive Ingredients:

Questions or comments?

+1 (646) 980-6461

Product Labeling

Made By Dentists™

Whitening

Toothpaste

Fresh Mint Flavor

Fluoride Anticavity Toothpaste

NET WT 4.2 Oz / 120 g

MADE IN THE USA

90 South Dale, Suite 8, Saint Paul,

Minnesota, USA 55102

Carton

Tube

res